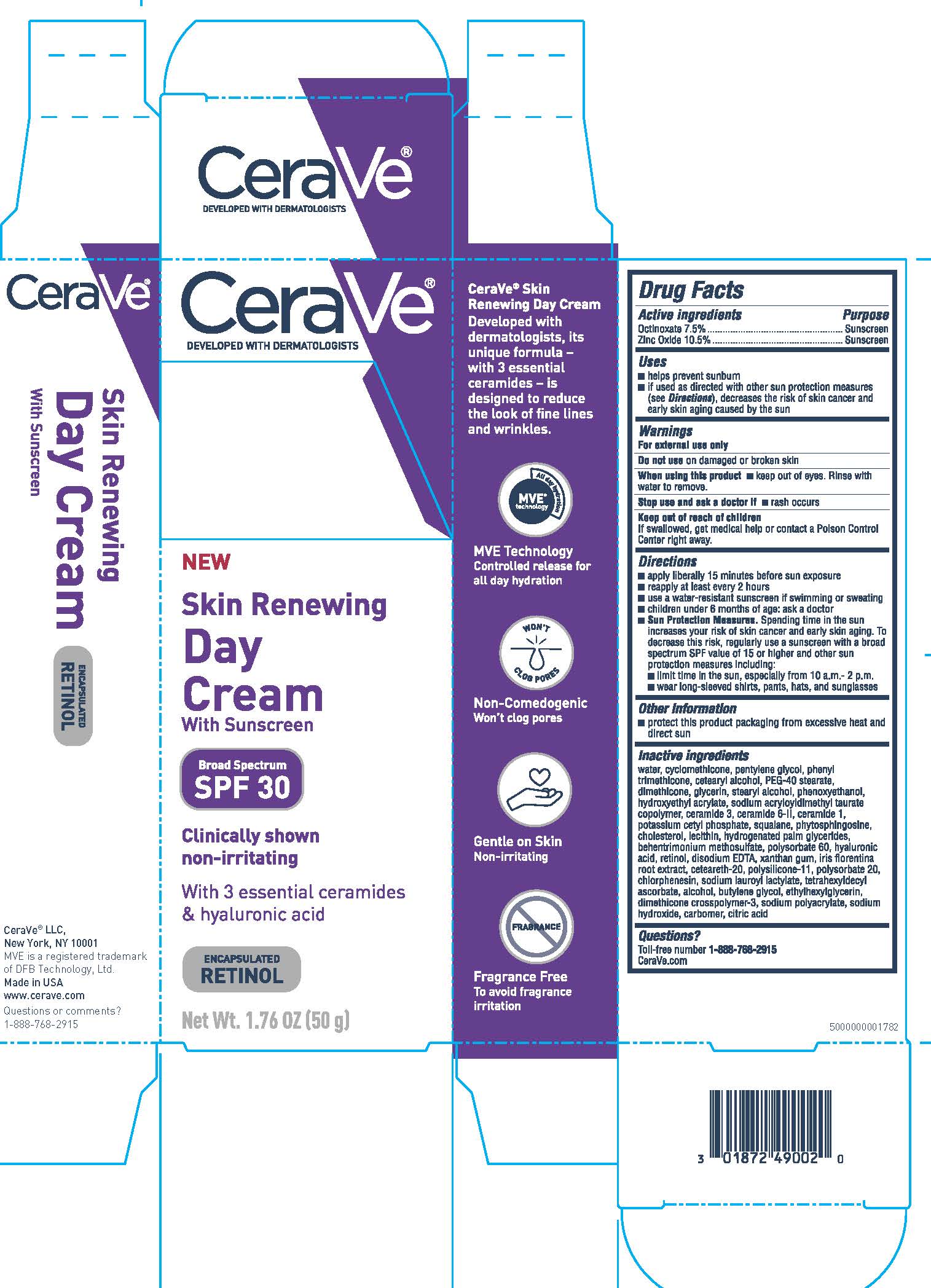 DRUG LABEL: CeraVe Developed with Dermatologists Skin Renewing Broad Spectrum SPF 30 Day
NDC: 49967-900 | Form: CREAM
Manufacturer: L'Oreal USA Products Inc.
Category: otc | Type: HUMAN OTC DRUG LABEL
Date: 20231231

ACTIVE INGREDIENTS: OCTINOXATE 75 mg/1 g; ZINC OXIDE 105 mg/1 g
INACTIVE INGREDIENTS: WATER; CYCLOMETHICONE; PENTYLENE GLYCOL; PHENYL TRIMETHICONE; CETOSTEARYL ALCOHOL; PEG-40 STEARATE; DIMETHICONE; GLYCERIN; STEARYL ALCOHOL; PHENOXYETHANOL; HYDROXYETHYL ACRYLATE/SODIUM ACRYLOYLDIMETHYL TAURATE COPOLYMER (100000 MPA.S AT 1.5%); CERAMIDE NP; CERAMIDE AP; CERAMIDE 1; POTASSIUM CETYL PHOSPHATE; SQUALANE; PHYTOSPHINGOSINE; CHOLESTEROL; LECITHIN, SOYBEAN; HYDROGENATED PALM GLYCERIDES; BEHENTRIMONIUM METHOSULFATE; POLYSORBATE 60; HYALURONIC ACID; RETINOL; EDETATE DISODIUM; XANTHAN GUM; IRIS GERMANICA VAR. FLORENTINA ROOT; POLYOXYL 20 CETOSTEARYL ETHER; DIMETHICONE/VINYL DIMETHICONE CROSSPOLYMER (SOFT PARTICLE); POLYSORBATE 20; CHLORPHENESIN; SODIUM LAUROYL LACTYLATE; TETRAHEXYLDECYL ASCORBATE; ALCOHOL; BUTYLENE GLYCOL; ETHYLHEXYLGLYCERIN; DIMETHICONE CROSSPOLYMER (450000 MPA.S AT 12% IN CYCLOPENTASILOXANE); SODIUM POLYACRYLATE (8000 MW); SODIUM HYDROXIDE; CARBOXYPOLYMETHYLENE; CITRIC ACID MONOHYDRATE

Drug Facts

Active ingredients

Octinoxate 7.5%

Zinc Oxide 10.5%

Purpose

Sunscreen

Sunscreen

Uses

- helps prevent sunburn
- if used as directed with other sun protection measures (see Directions), decreases the risk of skin cancer and early skin aging caused by the sun

Warnings

For external use only

Do not use on damaged or broken skin

When using this product keep out of eyes. Rinse with water to remove.

Stop use and ask a doctor if rash occurs

Keep out of reach of children.

If swallowed, get medical help or contact a Poison Control Center right away.

Directions

- apply liberally 15 minutes before sun exposure
- reapply at least every 2 hours
- use a water-resistant sunscreen if swimming or sweating
- children under 6 months of age: Ask a doctor
- Sun Protection Measures. Spending time in the sun increases your risk of skin cancer and early skin aging. To decrease this risk, regularly use a sunscreen with a broad spectrum SPF value of 15 or higher and other sun protection measures including: •limit time in the sun, especially from 10 a.m. – 2 p.m. •wear long-sleeved shirts, pants, hats, and sunglasses

Other information

protect this product packaging from excessive heat and direct sun

Inactive ingredients

water, cyclomethicone, pentylene glycol, phenyl trimethicone, cetearyl alcohol, PEG-40 stearate,

dimethicone, glycerin, stearyl alcohol, phenoxyethanol, hydroxyethyl acrylate, sodium acryloyldimethyl taurate copolymer, ceramide 3, ceramide 6-II, ceramide 1, potassium cetyl phosphate, squalane, phytosphingosine, cholesterol, lecithin, hydrogenated palm glycerides, behentrimonium methosulfate, polysorbate 60, hyaluronic acid, retinol, disodium EDTA, xanthan gum, iris florentina root extract, ceteareth-20, polysilicone-11, polysorbate 20, chlorphenesin, sodium lauroyl lactylate, tetrahexyldecyl

ascorbate, alcohol, butylene glycol, ethylhexylglycerin, dimethicone crosspolymer-3, sodium polyacrylate, sodium hydroxide, carbomer, citric acid

Questions?

Toll-free number 1-888-768-2915

CeraVe.com